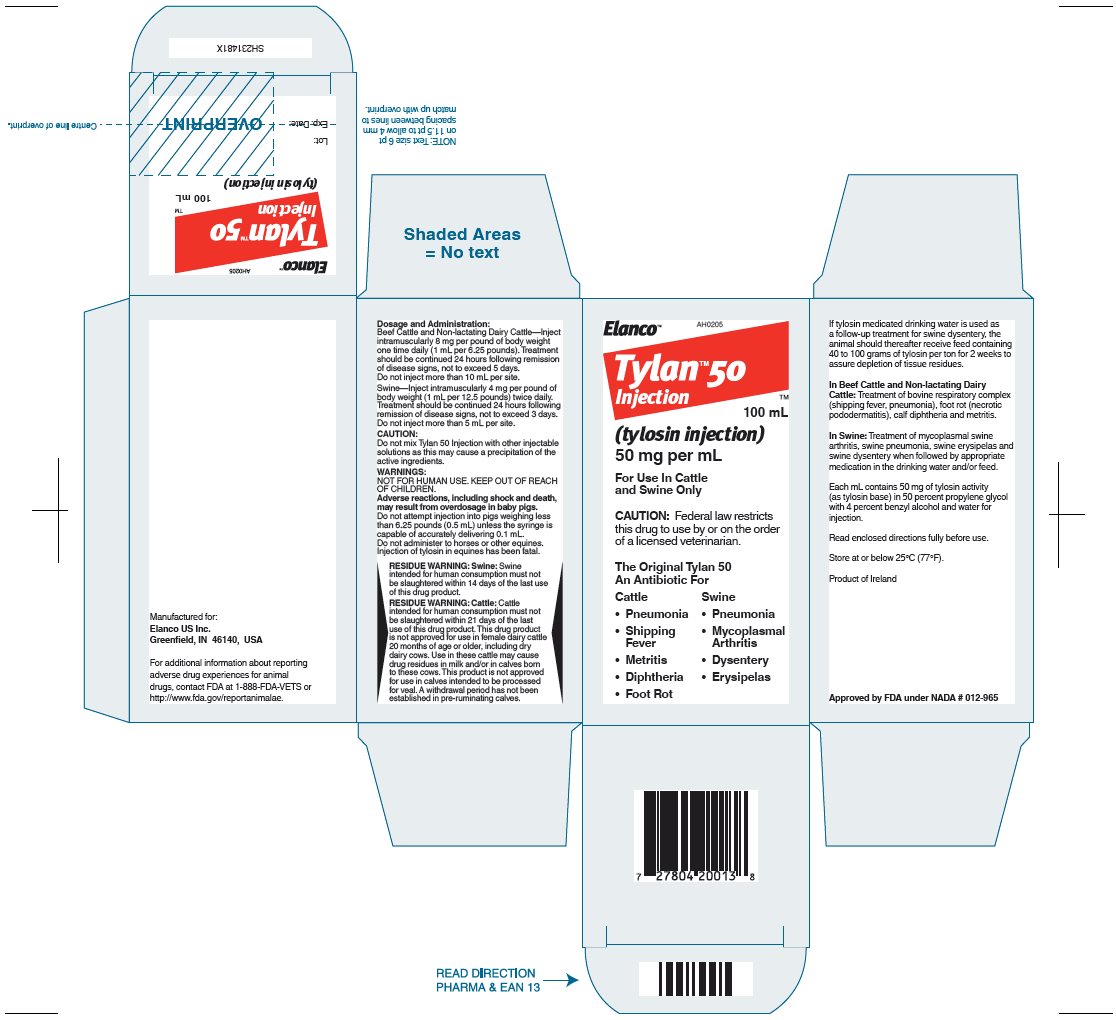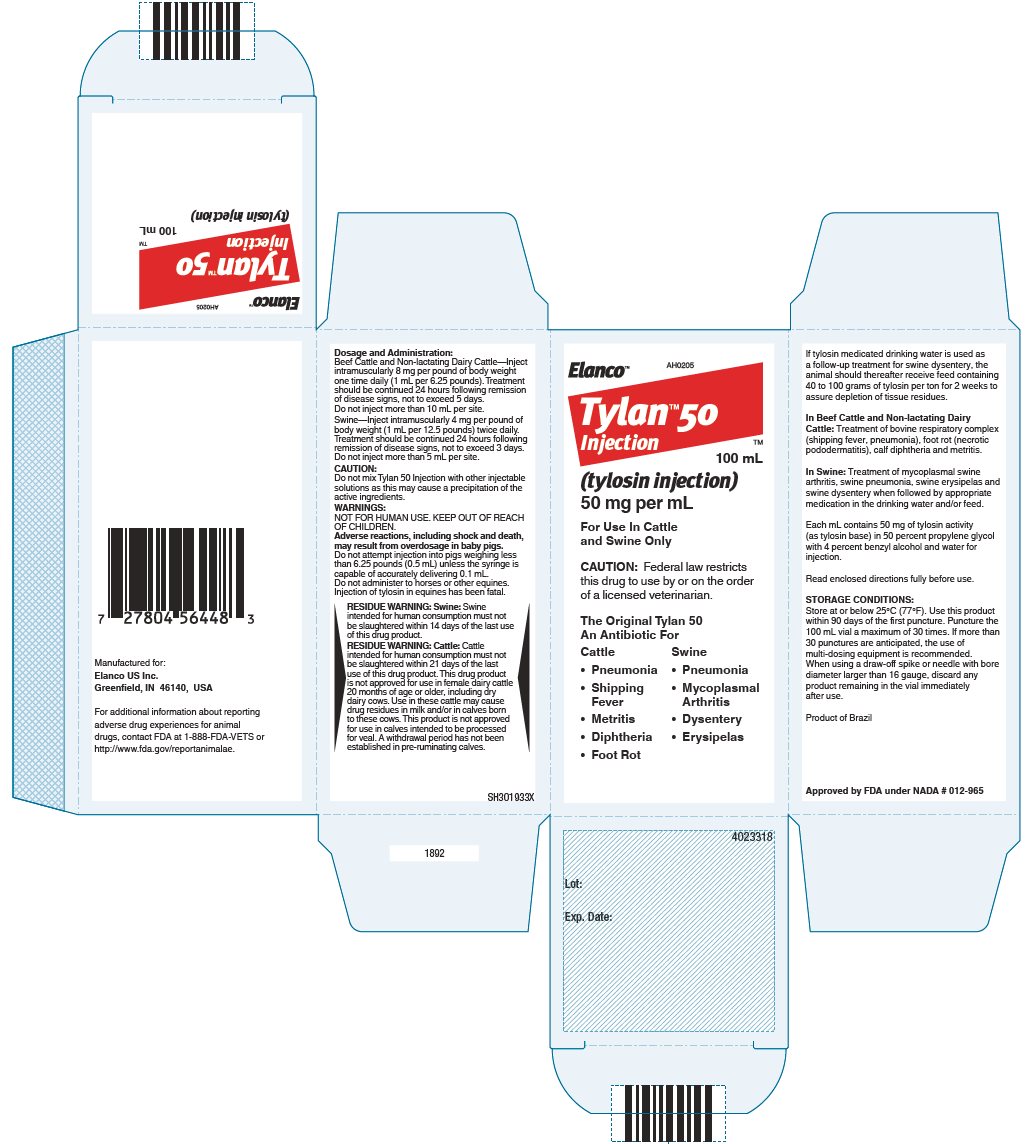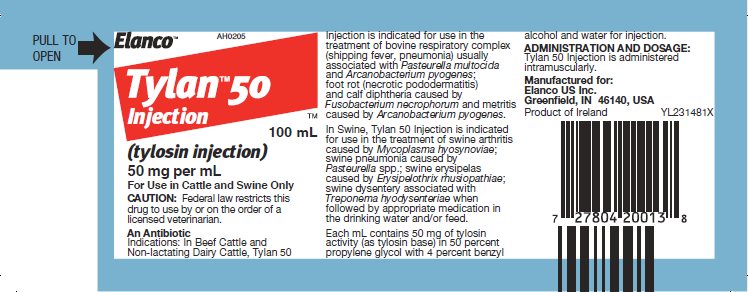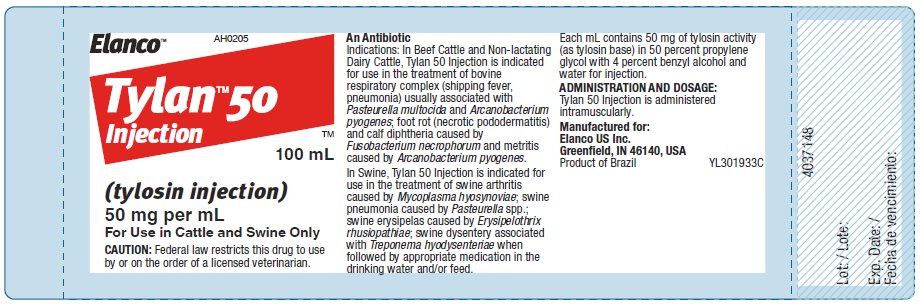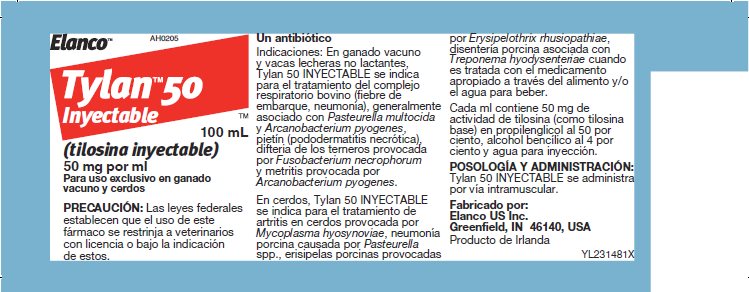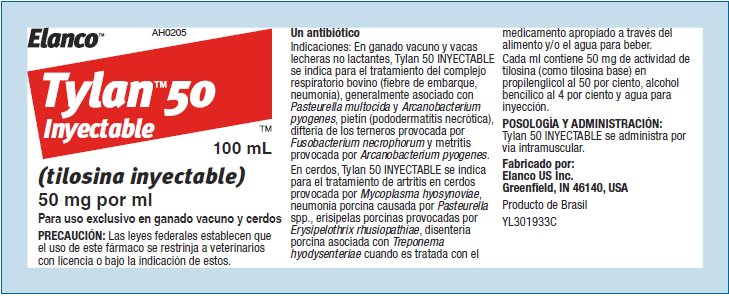 DRUG LABEL: Tylan 50
NDC: 58198-0205 | Form: INJECTION, SOLUTION
Manufacturer: Elanco US Inc.
Category: animal | Type: PRESCRIPTION ANIMAL DRUG LABEL
Date: 20250725

ACTIVE INGREDIENTS: tylosin 50 mg/1 mL

Elanco™

Tylan™ 50 Injection

(tylosin injection) 50 mg per mL

For Use In Cattle and Swine Only

An Antibiotic

Indications:

In Beef Cattle and Non-lactating Dairy Cattle, Tylan 50 Injection is indicated for use in the treatment of bovine respiratory complex (shipping fever, pneumonia) usually associated with Pasteurella multocida and Arcanobacterium pyogenes; foot rot (necrotic pododermatitis) and calf diphtheria caused by Fusobacterium necrophorum and metritis caused by Arcanobacterium pyogenes.

In Swine, Tylan 50 Injection is indicated for use in the treatment of swine arthritis caused by Mycoplasma hyosynoviae; swine pneumonia caused by Pasteurella spp.; swine erysipelas caused by Erysipelothrix rhusiopathiae; swine dysentery associated with Treponema hyodysenteriae when followed by appropriate medication in the drinking water and/or feed.

Each mL contains 50 mg of tylosin activity (as tylosin base) in 50 percent propylene glycol with 4 percent benzyl alcohol and water for injection.

ADMINISTRATION AND DOSAGE:

Tylan 50 Injection is administered intramuscularly.

BEEF CATTLE AND NON-LACTATING DAIRY CATTLE—Inject intramuscularly 8 mg per pound of body weight one time daily (1 mL per 6.25 pounds). Treatment should be continued 24 hours following remission of disease signs, not to exceed 5 days. Do not inject more than 10 mL per site.

This formulation is recommended for use in calves weighing less than 200 pounds.

SWINE—Inject intramuscularly 4 mg per pound of body weight (1 mL per 12.5 pounds) twice daily. Treatment should be continued 24 hours following remission of disease signs, not to exceed 3 days. Do not inject more than 5 mL per site.

Read accompanying directions fully before use.

CAUTION:

Do not mix Tylan 50 Injection with other injectable solutions as this may cause a precipitation of the active ingredients.

WARNINGS:

NOT FOR HUMAN USE. KEEP OUT OF REACH OF CHILDREN.

Adverse reactions, including shock and death, may result from overdosage in baby pigs.

Do not attempt injection into pigs weighing less than 6.25 pounds (0.5 mL) unless the syringe is capable of accurately delivering 0.1 mL.

Do not administer to horses or other equines. Injection of tylosin in equines has been fatal.

RESIDUE WARNING: Swine:

Swine intended for human consumption must not be slaughtered within 14 days of the last use of this drug product.

RESIDUE WARNING: Cattle:

Cattle intended for human consumption must not be slaughtered within 21 days of the last use of this drug product. This drug product is not approved for use in female dairy cattle 20 months of age or older, including dry dairy cows. Use in these cattle may cause drug residues in milk and/or in calves born to these cows. This product is not approved for use in calves intended to be processed for veal. A withdrawal period has not been established in pre-ruminating calves.

If tylosin medicated drinking water is used as a follow-up treatment for swine dysentery, the animal should thereafter receive feed containing 40 to 100 grams of tylosin per ton for 2 weeks to assure depletion of tissue residues.

STORAGE CONDITIONS:

Store at or below 25°C (77°F). Use this product within 90 days of the first puncture. Puncture the 100 mL vial a maximum of 30 times. If more than 30 punctures are anticipated, the use of multi-dosing equipment is recommended. When using a draw-off spike or needle with bore diameter larger than 16 gauge, discard any product remaining in the vial immediately after use.

Tylan, Elanco and the diagonal bar logo are trademarks of Elanco or its affiliates.

© 2025 Elanco or its affiliates

Approved by FDA under NADA # 012-965

For additional information about reporting adverse drug experiences for animal drugs, contact FDA at 1-888-FDA-VETS or http://www.fda.gov/reportanimalae.

Manufactured for:
Elanco US Inc.
Greenfield, IN 46140, US

Product of Ireland
AH0205
YL231481X

Product of Brazil
AH0205
YL301933C

Elanco™

Tylan™ 50 Inyectable

(tilosina inyectable) 50 mg por ml

Para uso exclusivo en ganado vacuno y cerdos

Un antibiótico:

Indicaciones:

En ganado vacuno y vacas lecheras no lactantes, Tylan 50 INYECTABLE se indica para el tratamiento del complejo respiratorio bovino (fiebre de embarque, neumonía), generalmente asociado con Pasteurella multicida y Arcanobacterium pyogenes, pietín (pododermatitis necrótica), difteria de los terneros provocada por Fusobacterium necrophorum y metritis provocada por Arcanobacterium pyogenes.

En cerdos, Tylan 50 INYECTABLE se indica para el tratamiento de artritis en cerdos provocada por Mycoplasma hyosynoviae, neumonía porcina causada por Pasteurella spp., erisipelas porcinas provocadas por Erysipelothrix rhusiopathiae, disentería porcina asociada con Treponema hyodysenteriae cuando es tratada con el medicamento apropiado a través del alimento y/o el agua para beber.

Cada ml contiene 50 mg de actividad de tilosina (como tilosina base) en propilenglicol al 50 por ciento, alcohol bencílico al 4 por ciento y agua para inyección.

POSOLOGÍA Y ADMINISTRACIÓN:

Tylan 50 INYECTABLE se administra por vía intramuscular.

GANADO VACUNO Y VACAS LECHERAS NO LACTANTES—Inyectar por vía intramuscular 8 mg por libra de peso corporal una vez al día (1 ml cada 6.25 libras). El tratamiento debe continuarse durante 24 horas luego de la remisión de los signos de la enfermedad sin extenderse más de 5 días. No aplicar más de 10 ml por lugar de inyección.

Se recomienda aplicar esta formulación en terneros que pesen menos de 200 libras.

CERDOS—Inyectar por vía intramuscular 4 mg por libra de peso corporal (1 ml cada 12.5 libras) dos veces al día. El tratamiento debe continuarse durante 24 horas luego de la remisión de los signos de la enfermedad sin extenderse más de 3 días. No aplicar más de 5 ml por lugar de inyección.

Leer todas las instrucciones adjuntas antes de usar.

PRECAUCIÓN:

No mezclar la inyección Tylan 50 con otras soluciones inyectables ya que esto puede ocasionar la precipitación de los principios activos.

ADVERTENCIAS:

ESTE PRODUCTO NO DEBE UTILIZARSE EN SERES HUMANOS. MANTENER FUERA DEL ALCANCE DE LOS NIÑOS.

Pueden ocurrir reacciones adversas, incluidos shock y muerte, en caso de sobredosis en crías de cerdos.

No administrar la inyección a cerdos que pesen menos de 6.25 libras (0.5 ml) a menos que la jeringa pueda administrar 0.1 ml de forma precisa.

No administrar a caballos u otros equinos. La inyección de tilosina en equinos ha resultado mortal.

ADVERTENCIA ACERCA DE RESIDUOS:

Ganado porcino: el ganado porcino previsto para consumo humano no se debe faenar durante los 14 días posteriores al último uso de este producto farmacológico.

ADVERTENCIA ACERCA DE RESIDUOS:

Ganado bovino: el ganado bovino previsto para consumo humano no se debe faenar durante los 21 días posteriores al último uso de este producto farmacológico. Este producto farmacológico no está aprobado para su uso en ganado bovino lechero hembra de 20 meses de edad o más, incluidas las vacas lecheras secas. El uso en este ganado bovino puede producir residuos farmacológicos en la leche y/o en los terneros nacidos de estas vacas. Este producto no está aprobado para el uso en terneros que se procesarán para carne de ternera. No se ha establecido un período de retiro del fármaco en terneros prerrumiantes.

Si se suministra agua para beber con tilosina como tratamiento de seguimiento para la disentería porcina, el animal debe recibir posteriormente alimento que contenga entre 40 y 100 gramos de tilosina por tonelada durante 2 semanas para garantizar la depleción de los residuos de tejidos.

CONDICIONES DE ALMACENAMIENTO:

Almacenar a una temperatura de 25 °C (77 °F) o inferior. Utilice este producto dentro de los 90 días posteriores a la primera punción. Perfore el vial de 100 ml un máximo de 30 veces. Si se anticipan más de 30 punciones, se recomienda el uso de equipo de dosificación. Cuando utilice una punta o aguja desprendible con un diámetro interior mayor que el calibre 16, deseche cualquier producto restante en el vial inmediatamente después de usarlo.

Tylan, Elanco y el logo de la barra diagonal son marcas de Elanco o sus afiliadas.

Aprobado por la FDA bajo NADA #012-965

Para obtener información adicional sobre cómo informar experiencias adversas de medicamentos para medicamentos animales, comuníquese con la FDA al 1-888-FDA-VETS o http://www.fda.gov/reportanimalae.

Fabricado por: Elanco US Inc.
Greenfield, IN 46140, USA

Producto de Irlanda
AH0205
YL231481X

Producto de Brasil
AH0205
YL301933C

Principal Display Panel - Tylan 50 Injection Carton Label

Elanco™

AH0205

Tylan™ 50
Injection

™

100 mL

(tylosin injection)

50 mg per mL

For Use In Cattle
and Swine Only

CAUTION: Federal law restricts
this drug to use by or on the order
of a licensed veterinarian.

The Original Tylan 50
An Antibiotic For

Cattle

- Pneumonia
- Shipping
  Fever
- Metritis
- Diphtheria
- Foot Rot

Swine

- Pneumonia
- Mycoplasmal
  Arthritis
- Dysentery
- Erysipelas

Principal Display Panel - Tylan 50 Injection Bottle Label

Elanco™

AH0205

Tylan™ 50
Injection

™

100 mL

(tylosin injection)

50 mg per mL

For Use in Cattle and Swine Only

CAUTION: Federal law restricts this drug to use
by or on the order of a licensed veterinarian.

Principal Display Panel - Tylan 50 Injection Spanish Bottle Label

Elanco™

AH0205

Tylan™ 50
Inyectable

™

100 mL

(tilosina inyectable)

50 mg por ml

Para uso exclusivo en ganado
vacuno y cerdos

PRECAUCIÓN: Las leyes federales
estabablecen que el uso de este
fármaco se restrinja a veterinarios
con licencia o bajo la indicación
de estos.